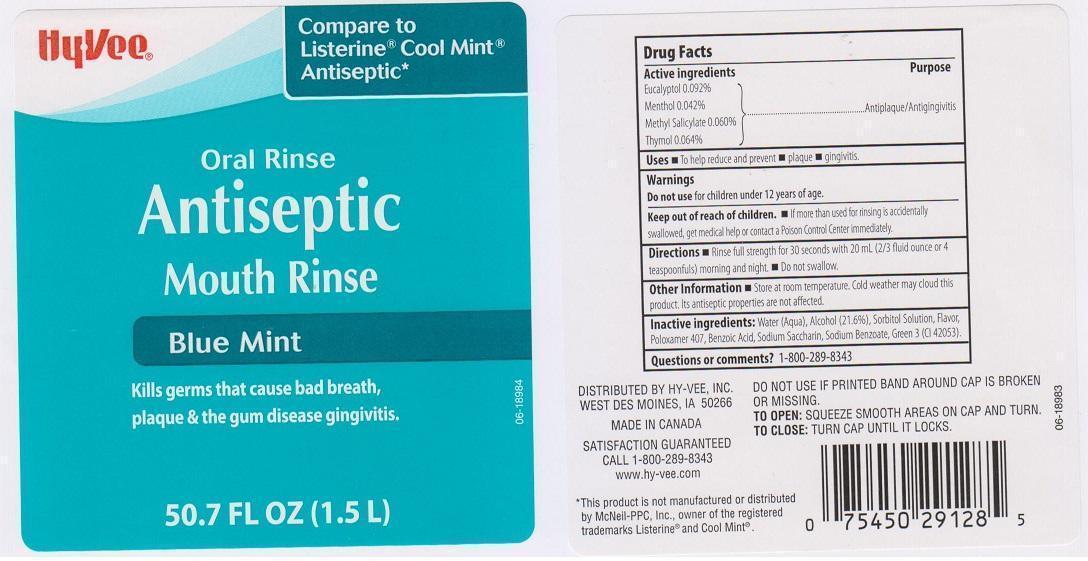 DRUG LABEL: HYVEE
NDC: 42507-559 | Form: LIQUID
Manufacturer: HYVEE INC
Category: otc | Type: HUMAN OTC DRUG LABEL
Date: 20150409

ACTIVE INGREDIENTS: EUCALYPTOL 0.92 mg/1 mL; MENTHOL 0.42 mg/1 mL; METHYL SALICYLATE 0.6 mg/1 mL; THYMOL 0.64 mg/1 mL
INACTIVE INGREDIENTS: WATER; ALCOHOL; SORBITOL; POLOXAMER 407; BENZOIC ACID; SACCHARIN SODIUM; SODIUM BENZOATE; FD&C GREEN NO. 3

DRUG FACTS

ACTIVE INGREDIENTS

EUCALYPTOL 0.092%, MENTHOL 0.042%, METHYL SALICYLATE 0.060%, THYMOL 0.064%

PURPOSE

ANTIPLAQUE/ANTIGINGIVITIS

USES

TO HELP REDUCE AND PREVENT

- PLAQUE
- GINGIVITIS

WARNINGS

DO NOT USE FOR CHILDREN UNDER 12 YEARS OF AGE

KEEP OUT OF REACH OF CHILDREN

IF MORE THAN USED FOR RINSING IS ACCIDENTALLY SWALLOWED, GET MEDICAL HELP OR CONTACT A POISON CONTROL CENTER IMMEDIATELY

DIRECTIONS

- RINSE FULL STRENGTH FOR 30 SECONDS WITH 20 ML (2/3 FLUID OUNCE OR 4 TEASPOONFULS) MORNING AND NIGHT
- DO NOT SWALLOW

DIRECTIONS

- RINSE FULL STRENGTH FOR 30 SECONDS, WITH 20 ML (2/3 FLUID OUNCES OR 4 TEASPOONFULS) MORNING AND NIGHT
- DO NOT SWALLOW

OTHER INFORMATION

STORE AT ROOM TEMPERATURE. COLD WEATHER MAY CLOUD THIS PRODUCT. ITS ANTISEPTIC PROPERTIES ARE NOT AFFECTED

INACTIVE INGREDIENTS

WATER (AQUA), ALCOHOL (21.6%), SORBITOL SOLUTION, FLAVOR, POLOXAMER 407, BENZOIC ACID, SODIUM SACCHARIN, SODIUM BENZOATE, GREEN 3 (CI 42053)

QUESTIONS OR COMMENTS?

1-800-289-8343